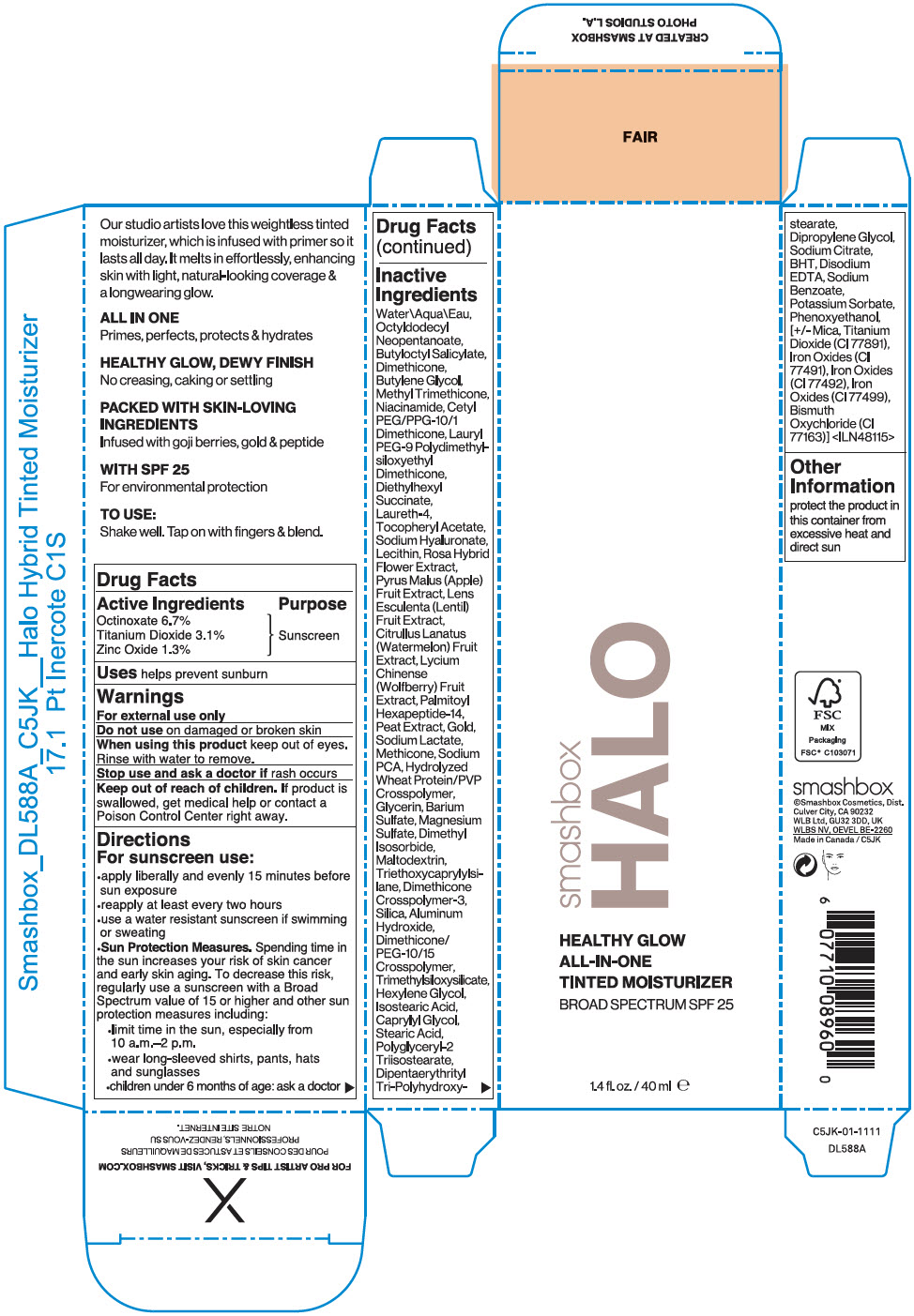 DRUG LABEL: SMASHBOX HALO HEALTHY GLOW ALL-IN-ONE TINTED MOISTURIZER BROAD SPECTRUM SPF 25
NDC: 10348-018 | Form: LIQUID
Manufacturer: SMASHBOX BEAUTY COSMETICS, INC
Category: otc | Type: HUMAN OTC DRUG LABEL
Date: 20241225

ACTIVE INGREDIENTS: OCTINOXATE 67 mg/1 mL; TITANIUM DIOXIDE 31 mg/1 mL; ZINC OXIDE 13 mg/1 mL
INACTIVE INGREDIENTS: OCTYLDODECYL NEOPENTANOATE; WATER; BUTYLOCTYL SALICYLATE; DIMETHICONE; BUTYLENE GLYCOL; METHYL TRIMETHICONE; NIACINAMIDE; LAURYL PEG-9 POLYDIMETHYLSILOXYETHYL DIMETHICONE; DIETHYLHEXYL SUCCINATE; LAURETH-4; .ALPHA.-TOCOPHEROL ACETATE; HYALURONATE SODIUM; APPLE; LENS CULINARIS FRUIT; WATERMELON; GOLD; SODIUM LACTATE; METHICONE (20 CST); SODIUM PYRROLIDONE CARBOXYLATE; GLYCERIN; BARIUM SULFATE; MAGNESIUM SULFATE, UNSPECIFIED FORM; DIMETHYL ISOSORBIDE; MALTODEXTRIN; TRIETHOXYCAPRYLYLSILANE; SILICON DIOXIDE; ALUMINUM HYDROXIDE; HEXYLENE GLYCOL; ISOSTEARIC ACID; CAPRYLYL GLYCOL; STEARIC ACID; POLYGLYCERYL-2 TRIISOSTEARATE; DIPENTAERYTHRITYL TRI-POLYHYDROXYSTEARATE; DIPROPYLENE GLYCOL; SODIUM CITRATE, UNSPECIFIED FORM; BUTYLATED HYDROXYTOLUENE; EDETATE DISODIUM ANHYDROUS; SODIUM BENZOATE; POTASSIUM SORBATE; PHENOXYETHANOL; MICA; FERRIC OXIDE RED; FERRIC OXIDE YELLOW; FERROSOFERRIC OXIDE; BISMUTH OXYCHLORIDE; CETYL PEG/PPG-10/1 DIMETHICONE (HLB 4)

SMASHBOX HALO HEALTHY GLOW ALL-IN-ONE TINTED MOISTURIZER BROAD SPECTRUM SPF 25

Drug Facts

Active Ingredients

Octinoxate 6.7%
Titanium Dioxide 3.1%
Zinc Oxide 1.3%

Purpose

Sunscreen

Uses

helps prevent sunburn

Warnings

For external use only

Do not use on damaged or broken skin

When using this product keep out of eyes. Rinse with water to remove.

Stop use and ask a doctor if rash occurs

Keep out of reach of children. If product is swallowed, get medical help or contact a Poison Control Center right away.

Directions

For sunscreen use:

- apply liberally and evenly 15 minutes before sun exposure
- reapply at least every two hours
- use a water resistant sunscreen if swimming or sweating
- Sun Protection Measures. Spending time in the sun increases your risk of skin cancer and early skin aging. To decrease this risk, regularly use a sunscreen with a Broad Spectrum value of 15 or higher and other sun protection measures including:
  - limit time in the sun, especially from 10 a.m.–2 p.m.
  - wear long-sleeved shirts, pants, hats and sunglasses
  - children under 6 months of age: ask a doctor

Inactive Ingredients

Water\Aqua\Eau, Octyldodecyl Neopentanoate, Butyloctyl Salicylate, Dimethicone, Butylene Glycol, Methyl Trimethicone, Niacinamide, Cetyl PEG/PPG-10/1 Dimethicone, Lauryl PEG-9 Polydimethyl-siloxyethyl Dimethicone, Diethylhexyl Succinate, Laureth-4, Tocopheryl Acetate, Sodium Hyaluronate, Lecithin, Rosa Hybrid Flower Extract, Pyrus Malus (Apple) Fruit Extract, Lens Esculenta (Lentil) Fruit Extract, Citrullus Lanatus (Watermelon) Fruit Extract, Lycium Chinense (Wolfberry) Fruit Extract, Palmitoyl Hexapeptide-14, Peat Extract, Gold, Sodium Lactate, Methicone, Sodium PCA, Hydrolyzed Wheat Protein/PVP Crosspolymer, Glycerin, Barium Sulfate, Magnesium Sulfate, Dimethyl Isosorbide, Maltodextrin, Triethoxycaprylylsilane, Dimethicone Crosspolymer-3, Silica, Aluminum Hydroxide, Dimethicone/PEG-10/15 Crosspolymer, Trimethylsiloxysilicate, Hexylene Glycol, Isostearic Acid, Caprylyl Glycol, Stearic Acid, Polyglyceryl-2 Triisostearate, Dipentaerythrityl Tri-Polyhydroxystearate, Dipropylene Glycol, Sodium Citrate, BHT, Disodium EDTA, Sodium Benzoate, Potassium Sorbate, Phenoxyethanol, [+/- Mica, Titanium Dioxide (CI 77891), Iron Oxides (CI 77491), Iron Oxides (CI 77492), Iron Oxides (CI 77499), Bismuth Oxychloride (CI 77163)] <ILN48115>

Other Information

protect the product in this container from excessive heat and direct sun

PRINCIPAL DISPLAY PANEL - 40 ml Tube Carton

smashbox
HALO

HEALTHY GLOW
ALL-IN-ONE
TINTED MOISTURIZER
BROAD SPECTRUM SPF 25

1.4 fl. oz./ 40 ml ℮